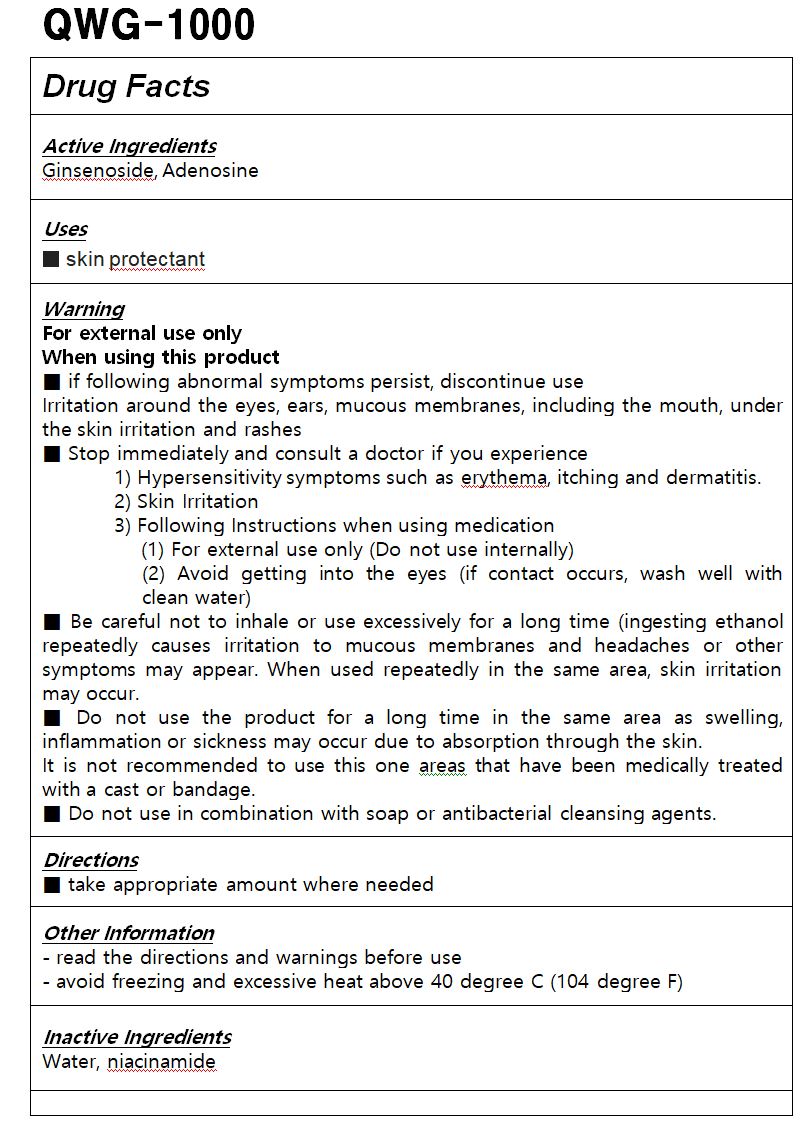 DRUG LABEL: QWG-1000
NDC: 83109-0001 | Form: LIQUID
Manufacturer: Institute of Quantum Bioscience
Category: otc | Type: HUMAN OTC DRUG LABEL
Date: 20221120

ACTIVE INGREDIENTS: GINSENOSIDES 0.04 g/100 mL; ADENOSINE 2 g/100 mL
INACTIVE INGREDIENTS: WATER

Drug Facts

ACTIVE INGREDIENT

ginsenoside, adenosine

PURPOSE

skin protectant

KEEP OUT OF REACH OF THE CHILDREN

INDICATIONS AND USAGE

take proper amount where needed

Keep out of reach of children.

Irritation around the eyes, ears, mucous membranes, including the mouth, under the skin irritation and rashes

Store in the room temperature

DOSAGE AND ADMINISTRATION

for oral use only

INACTIVE INGREDIENT

Purified water, adenosine